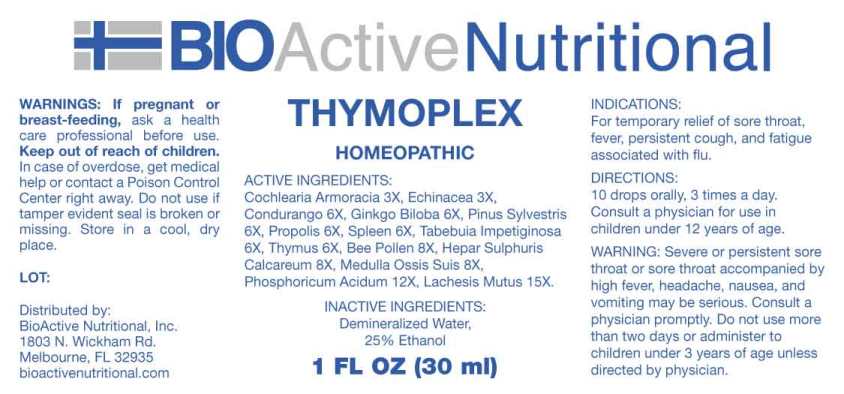 DRUG LABEL: Thymoplex
NDC: 43857-0564 | Form: LIQUID
Manufacturer: BioActive Nutritional, Inc.
Category: homeopathic | Type: HUMAN OTC DRUG LABEL
Date: 20241018

ACTIVE INGREDIENTS: HORSERADISH 3 [hp_X]/1 mL; ECHINACEA ANGUSTIFOLIA WHOLE 3 [hp_X]/1 mL; MARSDENIA CONDURANGO BARK 6 [hp_X]/1 mL; GINKGO 6 [hp_X]/1 mL; PINUS SYLVESTRIS LEAFY TWIG 6 [hp_X]/1 mL; PROPOLIS WAX 6 [hp_X]/1 mL; SUS SCROFA SPLEEN 6 [hp_X]/1 mL; HANDROANTHUS IMPETIGINOSUS WHOLE 6 [hp_X]/1 mL; BOS TAURUS THYMUS 6 [hp_X]/1 mL; BEE POLLEN 8 [hp_X]/1 mL; CALCIUM SULFIDE 8 [hp_X]/1 mL; SUS SCROFA BONE MARROW 8 [hp_X]/1 mL; PHOSPHORIC ACID 12 [hp_X]/1 mL; LACHESIS MUTA VENOM 15 [hp_X]/1 mL
INACTIVE INGREDIENTS: WATER; ALCOHOL

DRUG FACTS:

ACTIVE INGREDIENTS:

Cochlearia Armoracia 3X, Echinacea (Angustifolia) 3X, Condurango 6X, Ginkgo Biloba 6X, Pinus Sylvestris 6X, Propolis 6X, Spleen (suis) 6X, Tabebuia Impetiginosa 6X, Thymus (Bovine) 6X, Bee Pollen 8X, Hepar Sulphuris Calcareum 8X, Medulla Ossis Suis 8X, Phosphoricum Acidum 12X, Lachesis Mutus 15X.

INDICATIONS:

For temporary relief of sore throat, fever, persistent cough, and fatigue associated with flu.

WARNINGS:

If pregnant or breast-feeding, ask a health care professional before use.

Keep out of reach of children. In case of overdose, get medical help or contact a Poison Control Center right away. Do not use if tamper evident seal is broken or missing.Store in cool, dry place.

WARNING: Severe or persistent sore throat or sore throat accompanied by high fever, headache, nausea, and vomiting may be serious. Consult a physician promptly. Do not use more than two days or administer to children under 3 years of age unless directed by physician.

Keep out of reach of children. In case of overdose, get medical help or contact a Poison Control Center right away.

DIRECTIONS:

10 drops orally, 3 times a day. Consult a physician for use in children under 12 years of age.

INDICATIONS:

For temporary relief of sore throat, fever, persistent cough, and fatigue associated with flu.

INACTIVE INGREDIENTS:

Demineralized water, 25% Ethanol.

QUESTIONS:

Distributed by:

BioActive Nutritional, Inc.

1803 N. Wickham Rd.

Melbourne, FL 32935

bioactivenutritional.com

PACKAGE LABEL DISPLAY:

BioActive Homeopathic

THYMOPLEX

HOMEOPATHIC

1 FL OZ (30 ml)